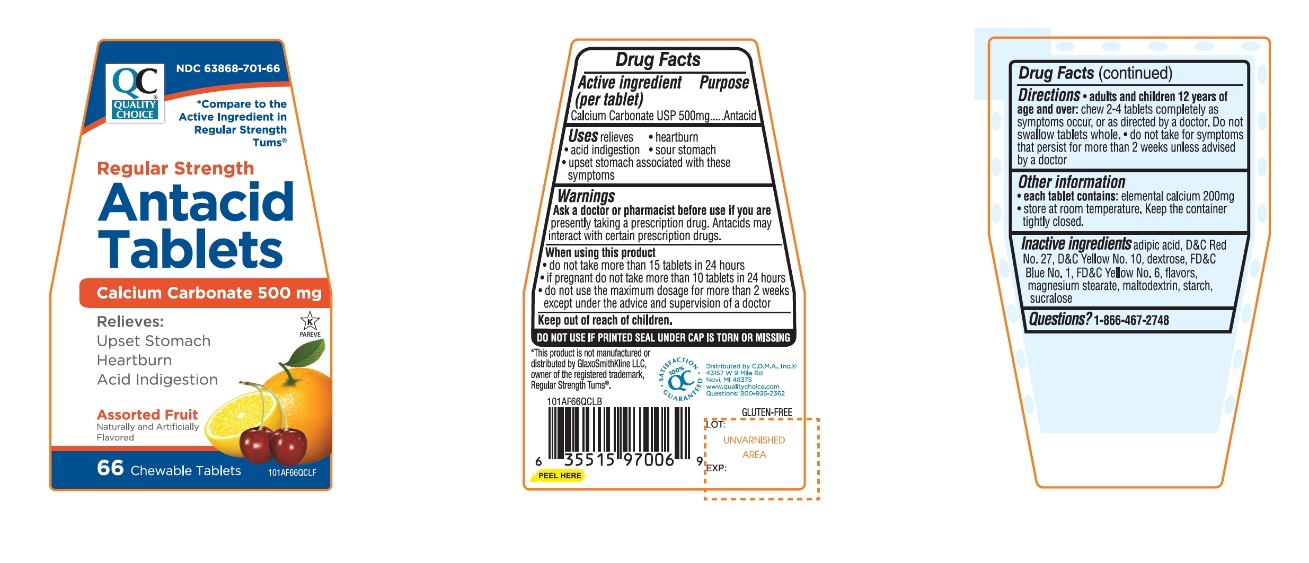 DRUG LABEL: Quality Choice Antacid

NDC: 63868-701 | Form: TABLET, CHEWABLE
Manufacturer: CHAIN DRUG MARKETING ASSOCIATION
Category: otc | Type: HUMAN OTC DRUG LABEL
Date: 20251203

ACTIVE INGREDIENTS: CALCIUM CARBONATE 500 mg/1 1
INACTIVE INGREDIENTS: ADIPIC ACID; D&C RED NO. 27; D&C YELLOW NO. 10; DEXTROSE, UNSPECIFIED FORM; FD&C BLUE NO. 1; FD&C YELLOW NO. 6; MAGNESIUM STEARATE; MALTODEXTRIN; STARCH, CORN; SUCRALOSE

Quality Choice Regular Strength Assorted Fruit Antacid Tablets

Active ingredient (per tablet)

Calcium Carbonate USP 500mg

Purpose

Antacid

Uses

relieves

- heartburn
- acid indigestion
- sour stomach
- upset stomach associated with these symptoms

Warnings

Ask a doctor or pharmacist before use if you arepresently taking a prescription drug. Antacids may interact with certain prescription drugs.

When using this product

- do not take more than 15 tablets in 24 hours
- if pregnant do not take more than 10 tablets in 24 hours
- do not use the maximum dosage for more than 2 weeks except under the advice and supervision of a doctor.

Directions

- adults and children 12 years of age and over:chew 2-4 tablets as symptoms occur, or as directed by a doctor
- do not take for symptoms that persist for more than 2 weeks unless advised by a doctor

Other information

- each tablet contains: elemental calcium 200mg
- store at room temperature. Keep the container tightly closed.

Inactive ingredients

adipic acid, D & C red # 27 lake, D&C yellow # 10 lake, dextrose, FD&C blue #1 lake, FD&C yellow #6 lake, flavors, magnesium stearate, maltodextrin, starch, sucralose.

Questions?

1-866-467-2748

Tamper Evident: Do not use if printed seal under cap is torn or missing

Package/Label Principal Display Panel

NDC # 63868-701-66

*Compare to the active ingredient in Regular Strength Tums®

Regular Strength

Antacid Tablets

Calcium Carbonate 500 mg

Relieves:

- Upset Stomach
- Heartburn
- Acid indigestion

ASSORTED FRUIT FLAVORS

K PAREVE

66 CHEWABLE TABLETS

GLUTEN- FREE

100% QC SATISFACTION GUARANTEED

1-888-423-0139.

Distributed by: C.D.M.A. Inc ©

43157 W 9 Mile Rd

Novi, MI 48375

www.qualitychoice.com

Questions: 248-449-9300

*This product is not manufactured or distributed by GlaxoSmithKline LLC, owner of the registered trademark, Regular Strength Tums®.